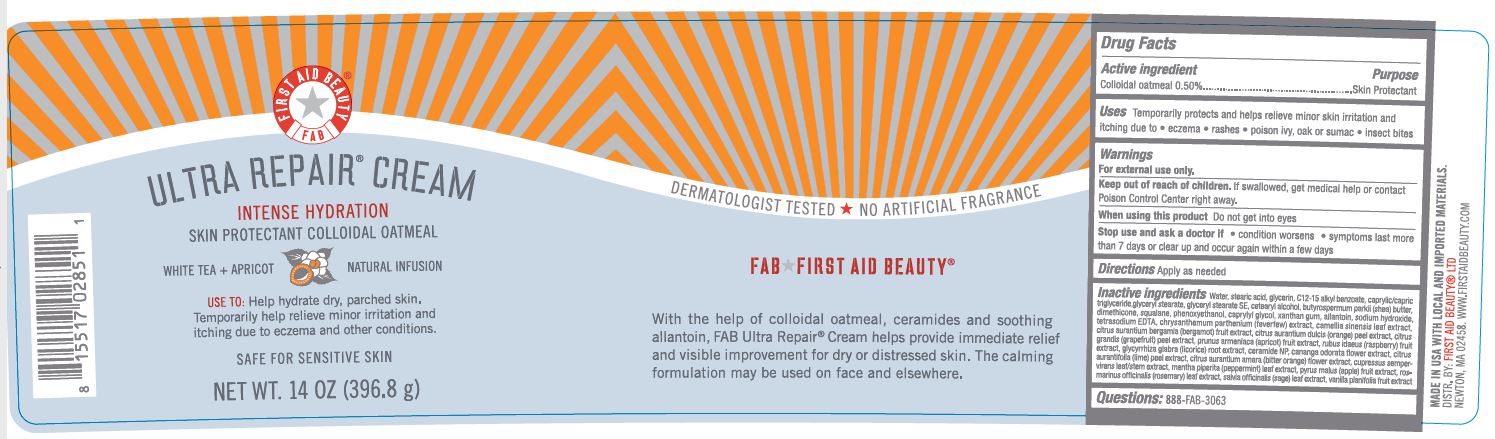 DRUG LABEL: First Aid Beauty FAB Ultra Repair Intense Hydration Skin Protectant White Tea and Apricot
NDC: 69423-564 | Form: CREAM
Manufacturer: The Procter & Gamble Manufacturing Company
Category: otc | Type: HUMAN OTC DRUG LABEL
Date: 20251218

ACTIVE INGREDIENTS: OATMEAL 0.5 g/100 g
INACTIVE INGREDIENTS: CUPRESSUS SEMPERVIRENS LEAFY TWIG; MENTHA PIPERITA LEAF; APPLE; SAGE; DIMETHICONE; CANANGA ODORATA FLOWER; CITRUS MAXIMA FRUIT RIND; TANACETUM PARTHENIUM WHOLE; CETOSTEARYL ALCOHOL; SQUALANE; EDETATE DISODIUM; GLYCERYL STEARATE SE; ALKYL (C12-15) BENZOATE; GREEN TEA LEAF; CAPRYLYL GLYCOL; SODIUM HYDROXIDE; PHENOXYETHANOL; SHEA BUTTER; GLYCYRRHIZA GLABRA; WATER; GLYCERIN; ALLANTOIN; GLYCERYL MONOSTEARATE; MEDIUM-CHAIN TRIGLYCERIDES; STEARIC ACID; XANTHAN GUM; ORANGE PEEL; CERAMIDE NP; BERGAMOT OIL; APRICOT; ROSEMARY OIL; VANILLA BEAN; RASPBERRY; LIME PEEL; CITRUS AURANTIUM FLOWER

First Aid Beauty FAB Ultra Repair Cream Skin Protectant White Tea and Apricot

Drug Facts

Active ingredients

Colloidal Oatmeal 0.5%

Purpose

Skin Protectant

Uses

- Temporarily protects and helps relieve minor skin irritation and itching due to eczema, rashes, poison ivy, oak or sumac, insect bites

Warnings

For external use only.

Keep out of reach of children. If swallowed, get medical help or contact a Poison Control Center right away.

WHEN USING

Do not get into eyes.

Stop use and ask a doctor if condition worsens, symptoms last more than 7 days or clear up and occur again within a few days

Directions

Apply as needed

INACTIVE INGREDIENT

Water, stearic acid, glycerin, c12-15 alkyl benzoate, caprylic/capric triglyceride, glyceryl stearate, glyceryl stearate SE, cetearyl alcohol, butyrospermum parkii (shea) butter, dimethicone, squalene, phenoxyethanol, caprylyl glycol. xanthan gum, allantoin, sodium hydroxide, tetrasodium EDTA, chrysanthemum parthenium (feverfew) extract, camellia sinensis leaf extract, citrus aurantium bergamia (bergamot) fruit extract, citrus aurantium dulcis (orange) peel extract, citrus grandis (grapefruit) peel extract, prunus armeniaca (apricot) fruit extract, rubus idaeus (raspberry) fruit extract, glycyrrhiza glabra (licorice) root extract, ceramide NP, cananga odorata flower extract, citrus aurantifolia (lime) peel extract, citrus aurantium amara (bitter orange) flower extract, cupressus sempervirens leaf/stem extract, mentha piperita (peppermint) leaf extract, pyrus malus (apple) fruit extract, rosmarinus officinalis (rosemary) leaf extract, salvia officinalis (sage) leaf extract, vanilla planifolia fruit extract.

Questions:

888-FAB-3063

MADE IN USA

FIRST AID BEAUTY LTD

NEWTON, MA 02458

WWW.FIRSTAIDBEAUTY.COM

PRINCIPAL DISPLAY PANEL - 14.0 oz (396.8 g)

First Aid Beauty

FAB

Ultra Repair® Cream

Intense Hydration

Skin Protectant Colloidal Oatmeal

White Tea + Apricto Natural Infusion

FIrst Aid Beauty ®

Net Wt. 14.0 oz (396.8 g)